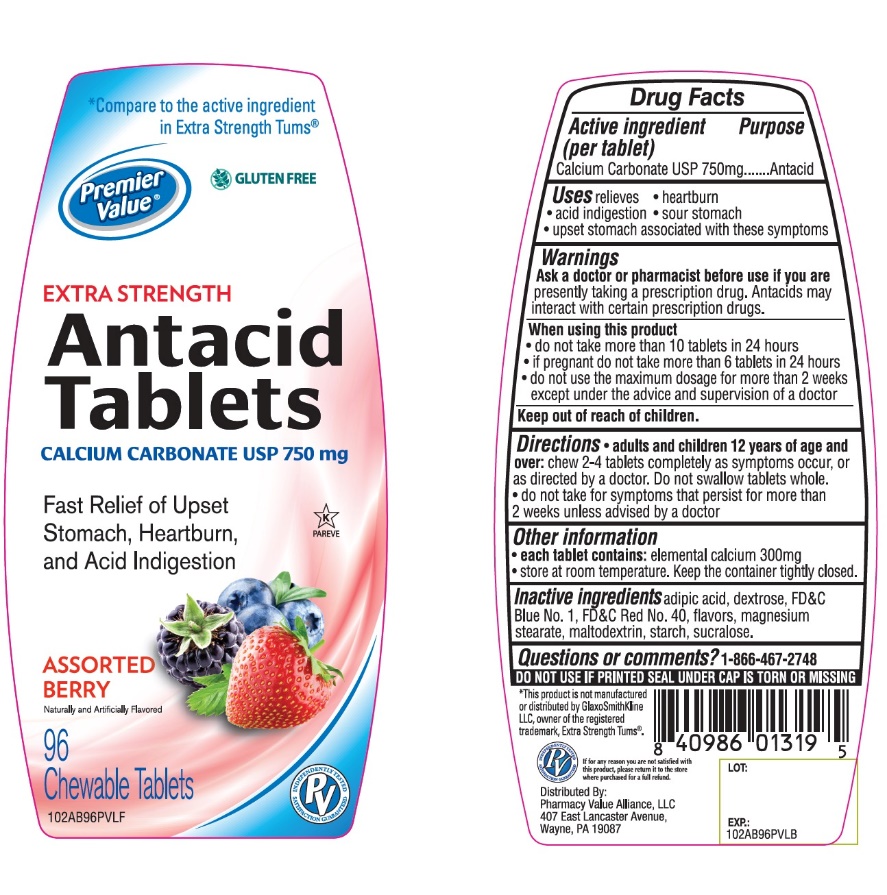 DRUG LABEL: Premier Value Extra Strength Chewable Antacid
NDC: 68016-667 | Form: TABLET, CHEWABLE
Manufacturer: Chain Drug Consortium
Category: otc | Type: HUMAN OTC DRUG LABEL
Date: 20220121

ACTIVE INGREDIENTS: CALCIUM CARBONATE 500 mg/1 1
INACTIVE INGREDIENTS: ADIPIC ACID; FD&C BLUE NO. 1; DEXTROSE, UNSPECIFIED FORM; MAGNESIUM STEARATE; MALTODEXTRIN; FD&C RED NO. 40; STARCH, CORN; SUCRALOSE

Drug Facts

Active ingredient

Calcium carbonate USP 750mg

Purpose

Antacid

Uses

relieves:

• heartburn

• sour stomach

• acid indigestion

• upset stomach associated with these symptoms

Warnings

Ask a doctor or pharmacist before use if you are taking a prescription drug. Antacids may interact with certain prescription drugs.

When using this product

• do not take more than 10 tablets in 24 hours

• do not use the maximum dosage for more than 2 weeks.

Directions

• Chew 2-4 tablets as symptoms occur, or as directed by a doctor.

Other Information

• Store below 30°C (86°F).

• Keep the container tightly closed

• For calcium and magnesium content see Supplement Facts.

Inactive ingredients

adipic acid, blue 1, dextrose, flavors, magnesium stearate, maltodextrin, red 40, starch, sucralose,

Safety sealed: Do not use if printed seal under cap is torn or missing

CALCIUM SUPPLEMENT

USES: As a daily source of extra calcium.

DIRECTIONS: Chew 2 tablets once or twice daily with a meal

Supplement Facts

Serving Size: 2 Tablets

Servings Per Container: 48

Amount Per Serving % | Daily Value
Calories 10
Sugars 2g
Calcium 600mg | 40%
Magnesium 2mg | less than 1%

Package/Label Principal Display Panel

Compare to the Active Ingredient in Tums*

Premier Value

Extra Strength

Calcium Antacid Tablets

Assorted Fruit Flavor

Calcium Rich

For Fast Relief of Heartburn, Acid Indigestion & Upset Stomach

96 Chewable Tablets

Distributed by

Chain Drug Consortium, LLC.

3301 N.W. Boca Raton Blvd.,

Suite 101, Boca Raton FL 33431

This product is not manufactured or distributed by GlaxoSmithKline, the distributor of Tums®